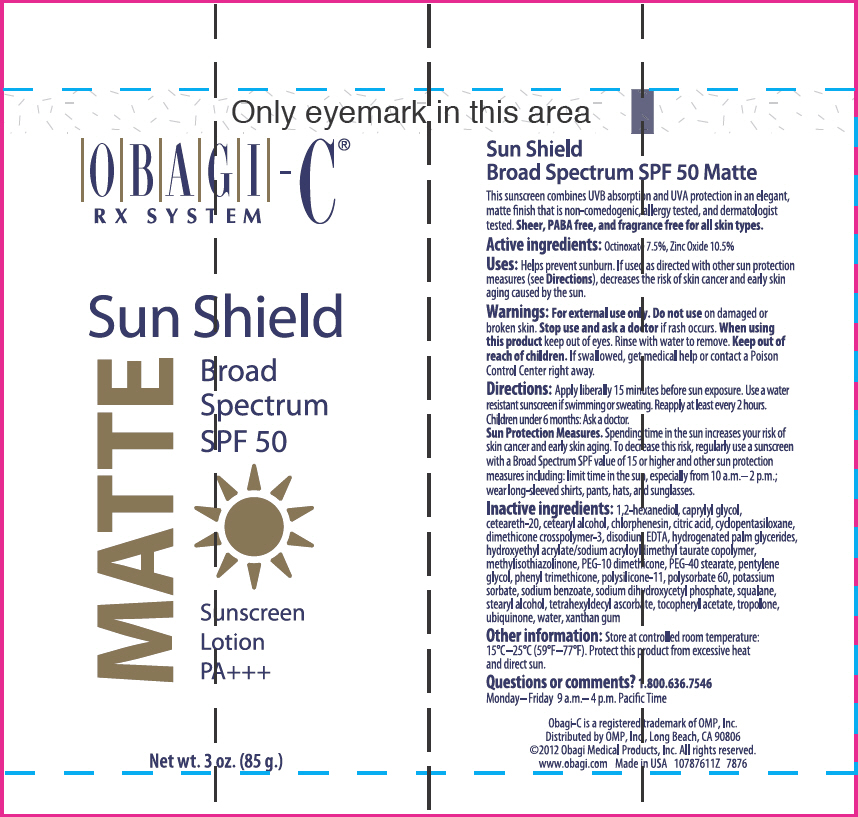 DRUG LABEL: OBAGI-C RX SYSTEM SUN SHIELD BROAD SPECTRUM SPF 50 
NDC: 62032-121 | Form: LOTION
Manufacturer: OMP, Inc.
Category: otc | Type: HUMAN OTC DRUG LABEL
Date: 20121219

ACTIVE INGREDIENTS: OCTINOXATE 75 mg/1 g; ZINC OXIDE 105 mg/1 g
INACTIVE INGREDIENTS: CYCLOMETHICONE 5; WATER; PEG-10 DIMETHICONE (600 CST); PENTYLENE GLYCOL; STEARYL ALCOHOL; POLYOXYL 20 CETOSTEARYL ETHER; PHENYL TRIMETHICONE; PEG-40 STEARATE; SODIUM DIHYDROXYCETYL PHOSPHATE; HYDROGENATED PALM GLYCERIDES; CITRIC ACID MONOHYDRATE; CETOSTEARYL ALCOHOL; .ALPHA.-TOCOPHEROL ACETATE; 1,2-HEXANEDIOL; CAPRYLYL GLYCOL; TROPOLONE; CHLORPHENESIN; XANTHAN GUM; POTASSIUM SORBATE; SODIUM BENZOATE; TETRAHEXYLDECYL ASCORBATE; UBIDECARENONE; EDETATE DISODIUM; METHYLISOTHIAZOLINONE; HYDROXYETHYL ACRYLATE/SODIUM ACRYLOYLDIMETHYL TAURATE COPOLYMER (45000 MPA.S AT 1%); SQUALANE; POLYSORBATE 60

OBAGI-C® RX SYSTEM SUN SHIELD BROAD SPECTRUM SPF 50
MATTE SUNSCREEN LOTION

Active ingredients

Octinoxate 7.5%, Zinc Oxide 10.5%

Uses

Helps prevent sunburn. If used as directed with other sun protection measures (see Directions), decreases the risk of skin cancer and early skin aging caused by the sun.

Warnings

For external use only.

Do not use on damaged or broken skin.

Stop use and ask a doctor if rash occurs.

When using this product keep out of eyes. Rinse with water to remove.

Keep out of reach of children. If swallowed, get medical help or contact a Poison Control Center right away.

Directions

Apply liberally 15 minutes before sun exposure. Use a water resistant sunscreen if swimming or sweating. Reapply at least every 2 hours. Children under 6 months: Ask a doctor.

Sun Protection Measures

Spending time in the sun increases your risk of skin cancer and early skin aging. To decrease this risk, regularly use a sunscreen with a Broad Spectrum SPF value of 15 or higher and other sun protection measures including: limit time in the sun, especially from 10 a.m.–2 p.m.; wear long-sleeved shirts, pants, hats, and sunglasses.

Inactive ingredients

1,2-hexanediol, caprylyl glycol, ceteareth-20, cetearyl alcohol, chlorphenesin, citric acid, cyclopentasiloxane, dimethicone crosspolymer-3, disodium EDTA, hydrogenated palm glycerides, hydroxyethyl acrylate/sodium acryloyldimethyl taurate copolymer, methylisothiazolinone, PEG-10 dimethicone, PEG-40 stearate, pentylene glycol, phenyl trimethicone, polysilicone-11, polysorbate 60, potassium sorbate, sodium benzoate, sodium dihydroxycetyl phosphate, squalane, stearyl alcohol, tetrahexyldecyl ascorbate, tocopheryl acetate, tropolone, ubiquinone, water, xanthan gum

Other information

Store at controlled room temperature: 15°C–25°C (59°F–77°F). Protect this product from excessive heat and direct sun.

Questions or comments?

1.800.636.7546

Monday–Friday 9 a.m.–4 p.m. Pacific Time

Distributed by OMP, Inc., Long Beach, CA 90806

PRINCIPAL DISPLAY PANEL - 85 g Tube Label

OBAGI-C®
RX SYSTEM

Sun Shield

MATTE

Broad
Spectrum
SPF 50

Sunscreen
Lotion
PA+++

Net wt. 3 oz. (85 g.)